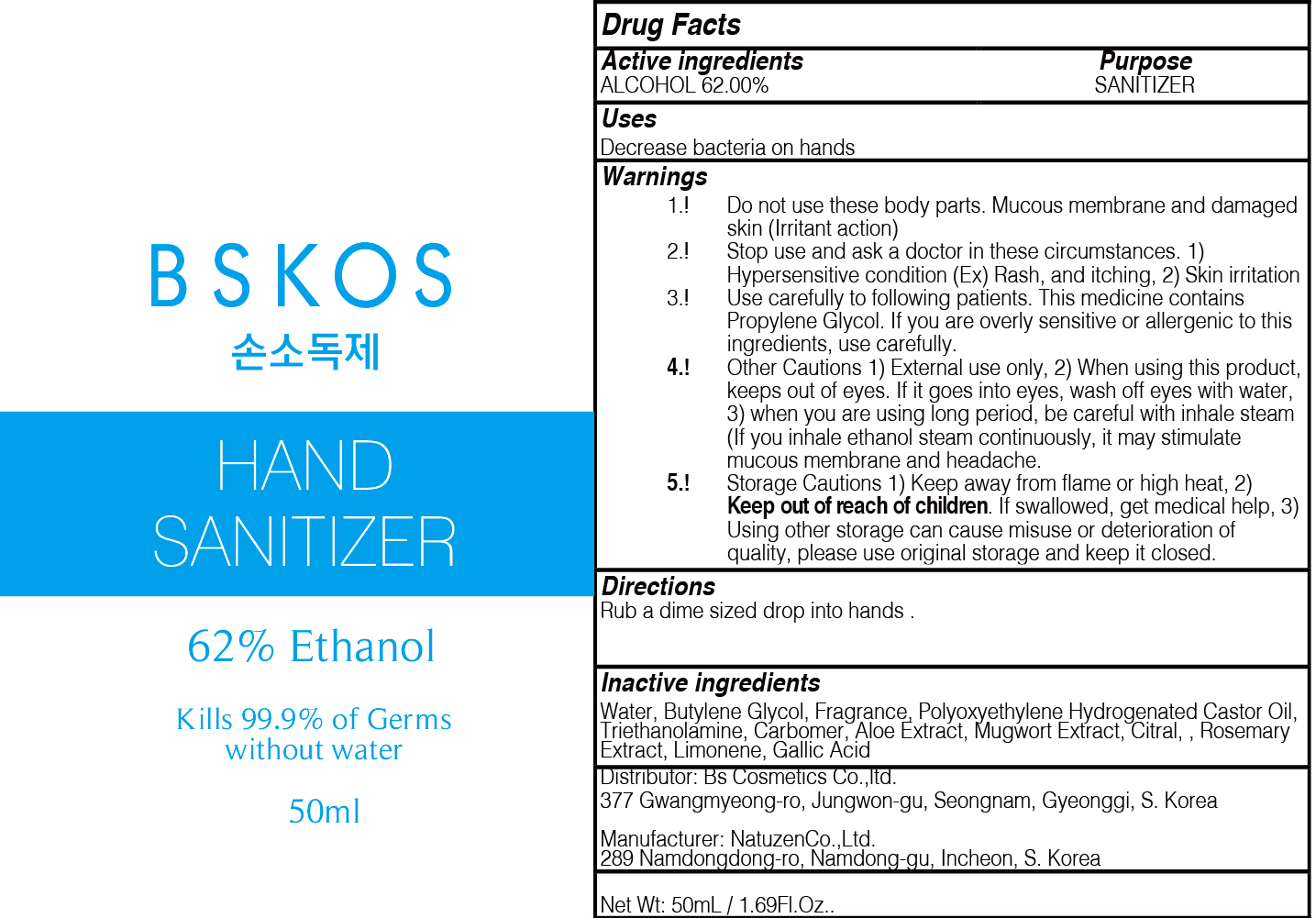 DRUG LABEL: Bskos Hand Sanitizer
NDC: 72600-260 | Form: GEL
Manufacturer: Bs Cosmetics Co.,ltd.
Category: otc | Type: HUMAN OTC DRUG LABEL
Date: 20200426

ACTIVE INGREDIENTS: ALCOHOL 31 g/50 mL
INACTIVE INGREDIENTS: Water; Butylene Glycol

Active Ingredients

Active ingredients: ALCOHOL 62.00%

INACTIVE INGREDIENT

Inactive ingredients:

Water, Butylene Glycol, Fragrance, Polyoxyethylene Hydrogenetated Caster Oil, Triethanolamine, Carbomer, Aloe Extract, Mugwort Extract, Citral,
Rosemary Extract, Limonene, Gallic Acid

Purpose

Purpose: SANITIZER

Warnings

1. Do not use these body parts. Mucous membrane and damaged skin (Irritant action)
2. Stop use and ask a doctor in these circumstances. 1) Hypersensitive condition (Ex) Rash, and itching, 2) Skin irritation
3. Use carefully to following patients. This medicine contains Propylene Glycol. If you are overly sensitive or allergenic to this ingredients, use carefully.
4. Other Cautions 1) External use only, 2) When using this product, keeps out of eyes. If it goes into eyes, wash off eyes with water, 3) when you are using long period, be careful with inhale steam (If you inhale ethanol steam continuously, it may stimulate mucous membrane and headache.
5. Storage Cautions 1) Keep away from flame or high heat, 2) Keep out of reach of children. If swallowed, get medical help, 3) Using other storage can cause misuse or deterioration of quality, please use original storage and keep it closed.

Keep out of reach of children. If swallowed, get medical help

Uses

Decrease bacteria on hands

Directions

Rub a dime sized drop into hands .